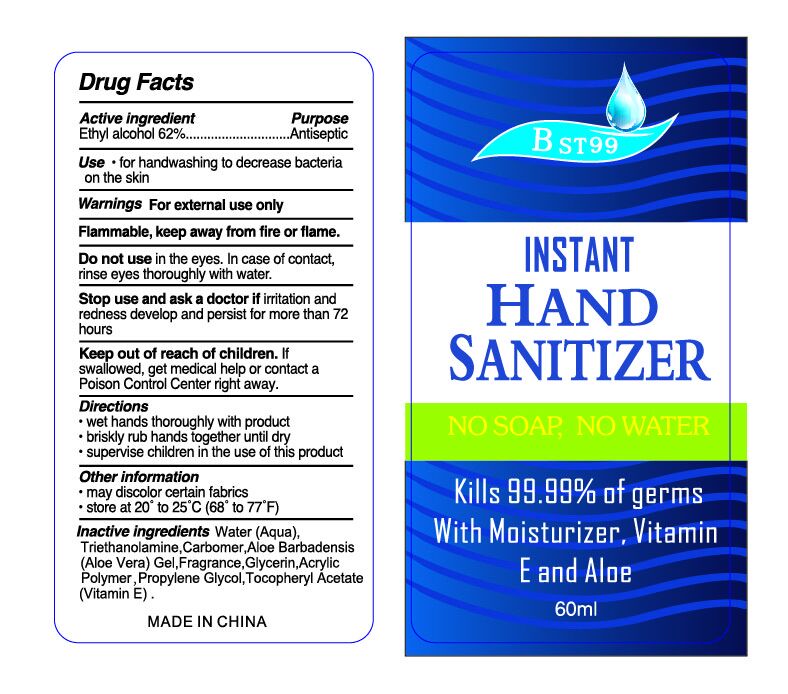 DRUG LABEL: BST99 Instant Hand Sanitizer
NDC: 52174-003 | Form: LIQUID
Manufacturer: Ningbo BST Clean And Care Products Co., Ltd
Category: otc | Type: HUMAN OTC DRUG LABEL
Date: 20200505

ACTIVE INGREDIENTS: ALCOHOL 62 mL/100 mL
INACTIVE INGREDIENTS: WATER; ALOE VERA LEAF; CARBOMER HOMOPOLYMER TYPE C; TROLAMINE; GLYCERIN; PROPYLENE GLYCOL; .ALPHA.-TOCOPHEROL ACETATE

Label Content

Active Ingredient:

Alcohol 62%

Purpose:

Antisptic

Usage:

For handwashing to decrease bacterial on the skin

DOSAGE AND ADMINISTRATION

Usage:

Wash hand thoroughly with product

Briskly rub hands together until dry.

Supervise children in the use of this product

Drug Facts
Water, triethanolamine, glycerin, propylene glycol, aloe barbadensis gel, carbomer, fragrance, acrylic polymer, Tocopherol Acetate (Vitamin E)

Warnings For external use only

Do not use in the eyes. In case of contact, flush thoroughly with water.
Stop use and ask a doctor when irritation and redness develop and persist for more than 72 hours.
Keep away from fire or flame. Flammable.

Keep out of reach of children. If swallowed, contact a physician or a poison control center immediately.